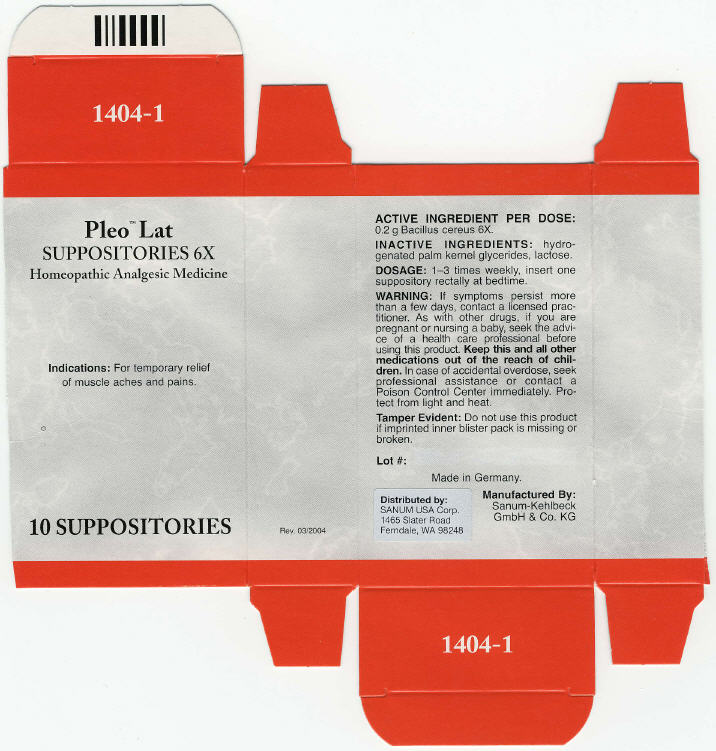 DRUG LABEL: Pleo Lat
NDC: 60681-1404 | Form: SUPPOSITORY
Manufacturer: Sanum Kehlbeck GmbH & Co. KG
Category: homeopathic | Type: HUMAN OTC DRUG LABEL
Date: 20091013

ACTIVE INGREDIENTS: bacillus cereus 6 [hp_X]/1 1
INACTIVE INGREDIENTS: lactose

Pleo™ Lat
SUPPOSITORIES 6X

Homeopathic Analgesic Medicine

10 SUPPOSITORIES

Indications

For temporary relief of muscle aches and pains.

ACTIVE INGREDIENT PER DOSE

0.2 g Bacillus cereus 6X.

INACTIVE INGREDIENTS

hydrogenated palm kernel glycerides, lactose.

DOSAGE

1–3 times weekly, insert one suppository rectally at bedtime.

WARNING

If symptoms persist more than a few days, contact a licensed practitioner. As with other drugs, if you are pregnant or nursing a baby, seek the advice of a health care professional before using this product.

KEEP OUT OF REACH OF CHILDREN

Keep this and all other medications out of the reach of children. In case of accidental overdose, seek professional assistance or contact a Poison Control Center immediately.

STORAGE AND HANDLING

Protect from light and heat.

Tamper Evident

Do not use this product if imprinted inner blister pack is missing or broken.

Made in Germany.

Distributed by:
SANUM USA Corp.
1465 Slater Road
Ferndale, WA 98248

Manufactured By:
Sanum-Kehlbeck
GmbH & Co. KG

Rev. 03/2004

PRINCIPAL DISPLAY PANEL - 10 Suppositories Carton

Pleo™ Lat
SUPPOSITORIES 6X

Homeopathic Analgesic Medicine

Indications: For temporary relief
of muscle aches and pains.

10 SUPPOSITORIES